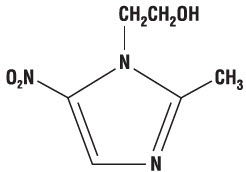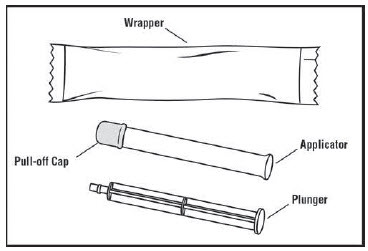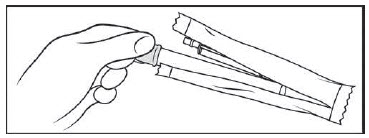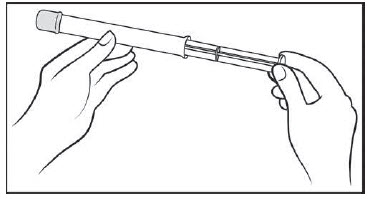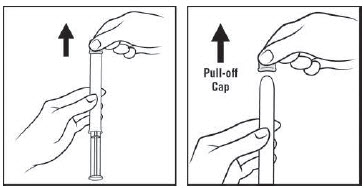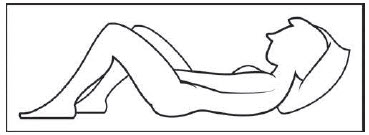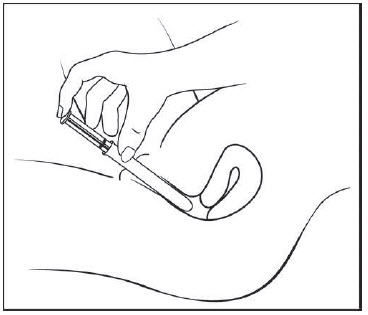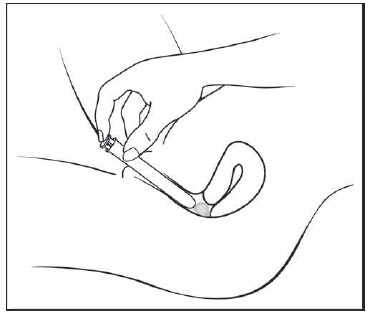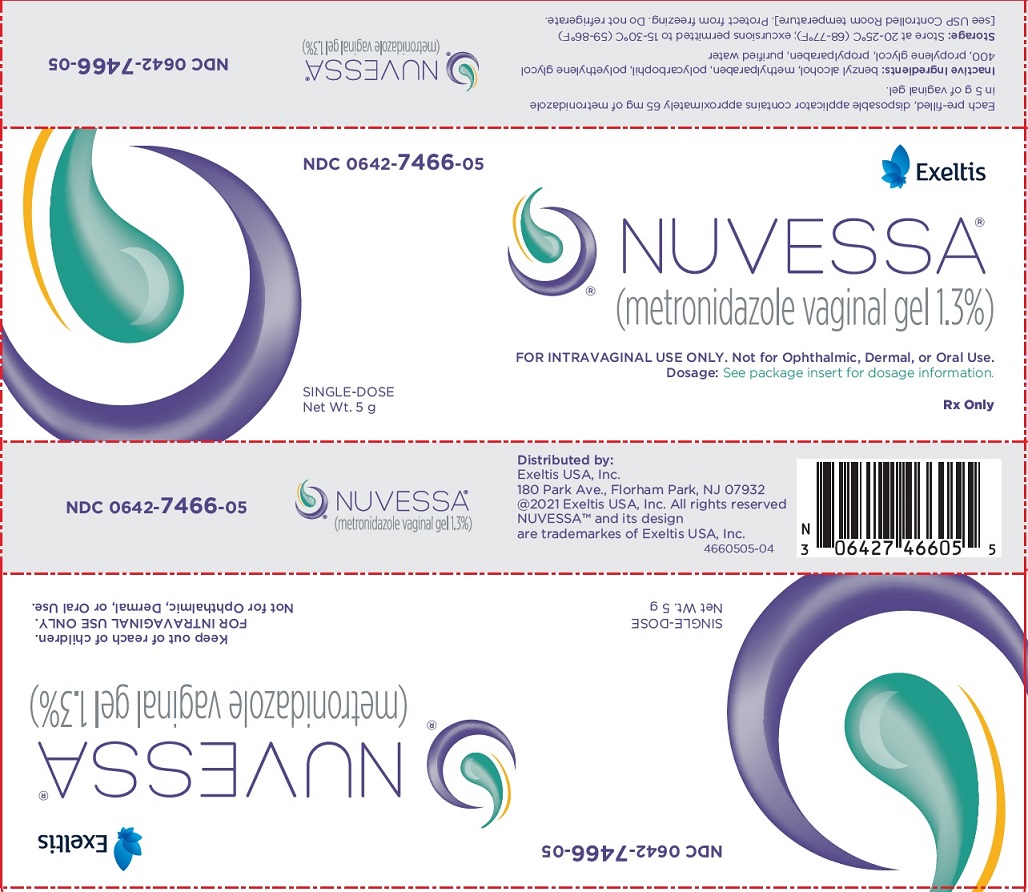 DRUG LABEL: Nuvessa
NDC: 0642-7466 | Form: GEL
Manufacturer: Exeltis USA, Inc.
Category: prescription | Type: HUMAN PRESCRIPTION DRUG LABEL
Date: 20231110

ACTIVE INGREDIENTS: METRONIDAZOLE 65 mg/5 g
INACTIVE INGREDIENTS: WATER; BENZYL ALCOHOL; METHYLPARABEN; POLYCARBOPHIL; POLYETHYLENE GLYCOL 400; PROPYLENE GLYCOL; PROPYLPARABEN

HIGHLIGHTS OF PRESCRIBING INFORMATION

These highlights do not include all the information needed to use NUVESSA safely and effectively. See full prescribing information for NUVESSA.
NUVESSA® (metronidazole vaginal gel 1.3%)
Initial U.S. Approval: 1963

1 INDICATIONS AND USAGE

NUVESSA is a nitroimidazole antimicrobial indicated for the treatment of bacterial vaginosis in females 12 years of age and older. (1)

2 DOSAGE AND ADMINISTRATION

- A single-dose, pre-filled disposable applicator administered once intravaginally at bedtime. (2)
- NUVESSA is not for ophthalmic, dermal, or oral use. (2)

3 DOSAGE FORMS AND STRENGTHS

Vaginal gel: 65 mg of metronidazole in 5 grams of gel (1.3%) in a prefilled applicator (3)

4 CONTRAINDICATIONS

- History of hypersensitivity to metronidazole, parabens, other ingredients of the formulation, or other nitroimidazole derivatives (4.1)
- Concomitant use of disulfiram or within 2 weeks of disulfiram (4.2, 7.1)
- Concomitant use of alcohol (4.3, 7.2)

5 WARNINGS AND PRECAUTIONS

- Central and peripheral nervous system effects: Convulsive seizures and peripheral neuropathy have been reported in patients treated with oral or intravenous metronidazole. Discontinue promptly if abnormal neurologic signs develop (5.1)
- Interference with laboratory tests: Metronidazole may interfere with certain serum chemistry laboratory values. (5.3)

6 ADVERSE REACTIONS

The most common adverse reactions observed in adult clinical studies (incidence ≥1%) were vulvovaginal candidiasis, headache, vulvovaginal pruritus, nausea, diarrhea, and dysmenorrhea.

The most common adverse reactions observed in pediatric clinical studies (incidence ≥1%) was vulvovaginal discomfort. (6.1)

To report SUSPECTED ADVERSE REACTIONS, contact Exeltis USA, Inc., at 1-877-324-9349 or FDA at 1-800-FDA-1088 or www.fda.gov/medwatch.

7 DRUG INTERACTIONS

- Warfarin and other coumarin anticoagulants: Prolonged anticoagulant effects of warfarin and other coumarin anticoagulants have been reported with co-administration of oral metronidazole. (7.3)
- Lithium: Elevated plasma lithium concentrations have been reported with oral metronidazole. (7.4)

8 USE IN SPECIFIC POPULATIONS

Lactation: A lactating patient may pump and discard breast milk during treatment and for 48 hours after the last dose. (8.2)

FULL PRESCRIBING INFORMATION

1 INDICATIONS AND USAGE

NUVESSA is indicated for the treatment of bacterial vaginosis in females 12 years of age and older.

2 DOSAGE AND ADMINISTRATION

A single-dose, pre-filled disposable applicator (which delivers approximately 5 g of gel containing 65 mg of metronidazole) administered once intravaginally. NUVESSA should be administered at bedtime.

NUVESSA is not for ophthalmic, dermal or oral use.

3 DOSAGE FORMS AND STRENGTHS

Vaginal gel (1.3%) containing 65 mg of metronidazole in 5 grams of gel in a pre-filled applicator.

4 CONTRAINDICATIONS

4.1 Hypersensitivity

NUVESSA is contraindicated in persons who have shown hypersensitivity to metronidazole, parabens, other ingredients of the formulation, or other nitroimidazole derivatives.

4.2 Use of Disulfiram

Psychotic reactions have been reported with co-administration of disulfiram and oral metronidazole. Do not administer concurrently with or within 2 weeks of disulfiram.

4.3 Concomitant Alcohol

Disulfiram-like reactions to alcohol have been reported with co-administration of oral metronidazole; do not consume ethanol or propylene glycol, during and for at least 24 hours following treatment.

5 WARNINGS AND PRECAUTIONS

5.1 Central and Peripheral Nervous System Effects

Convulsive seizures, encephalopathy, aseptic meningitis, optic and peripheral neuropathy, the latter characterized mainly by numbness or paresthesia of an extremity, have been reported in patients treated with oral or intravenous metronidazole. NUVESSA should be administered with caution to patients with central nervous system diseases. Discontinue promptly if abnormal neurologic signs develop.

5.2 Carcinogenicity in Animals

Metronidazole has been shown to be carcinogenic at high doses administered orally in mice and rats [see Nonclinical Toxicology (13.1)] . Unnecessary use of metronidazole should be avoided. Use of NUVESSA should be reserved for the treatment of bacterial vaginosis [see Indications and Usage (1)].

5.3 Drug/Laboratory Test Interactions

Metronidazole may interfere with certain types of determinations of serum chemistry values, such as aspartate aminotransferase (AST, SGOT), alanine aminotransferase (ALT, SGPT), lactate dehydrogenase (LDH), triglycerides, and glucose hexokinase. Values of zero may be observed. All of the assays in which interference has been reported involve enzymatic coupling of the assay to oxidation reduction of nicotinamide-adenine dinucleotides (NAD + NADH). Interference is due to the similarity in absorbance peaks of NADH (340 nm) and metronidazole (322 nm) at pH 7.

6 ADVERSE REACTIONS

Because clinical trials are conducted under widely varying conditions, adverse reaction rates observed in clinical trials of a drug cannot be directly compared to rates in the clinical trials of another drug and may not reflect the rates observed in practice.

6.1 Clinical Trials Experience

Clinical Trial Experience in Adult Subjects

The safety of NUVESSA was evaluated in a randomized, double-blind, vehicle-controlled study in subjects with bacterial vaginosis. A total of 321 non-pregnant females with a mean age of 33.4 years (range 18 to 67 years) received NUVESSA. Subjects were primarily Black/African American (58.3%) or White (39.3%). Subjects administered a single dose of NUVESSA at bedtime on the first day of the study.

There were no deaths or serious adverse reactions in this trial. Adverse reactions were reported by 19.0% of subjects treated with NUVESSA versus 16.1% of subjects treated with Vehicle Gel.

Adverse reactions occurring in ≥1% of subjects receiving NUVESSA were: vulvovaginal candidiasis (5.6%), headache (2.2%), vulvovaginal pruritus (1.6%), nausea (1.6%), diarrhea (1.2%), and dysmenorrhea (1.2%). No subjects discontinued treatment due to adverse reactions.

Clinical Trial Experience in Pediatric Subjects

The safety of NUVESSA was evaluated in a multicenter, open-label study evaluating the safety and tolerability of NUVESSA in 60 pediatric subjects between the ages of 12 and less than 18 years old all of whom were treated with a single dose of NUVESSA administered once at bedtime intravaginally. Most subjects in this study were either Black/African-American, non-Hispanic (47%) or Hispanic (35%).

Safety in pediatric female subjects aged 12 to less than 18 years old was comparable to adult women. No deaths occurred and no subjects discontinued treatment due to adverse reactions. Adverse reactions occurring in ≥ 1% of pediatric subjects included: vulvovaginal discomfort (2%).

6.2 Other Metronidazole Formulations

Other Vaginal Formulations

Other reactions that have been reported in association with the use of other formulations of metronidazole vaginal gel include: unusual taste and decreased appetite.

Topical (Dermal) Formulations

Other reactions that have been reported in association with the use of topical (dermal) formulations of metronidazole include skin irritation, transient skin erythema, and mild skin dryness and burning. None of these adverse reactions exceeded an incidence of 2% of patients.

Oral and Parenteral Formulations

The following adverse reactions and altered laboratory tests have been reported with the oral or parenteral use of metronidazole:

Cardiovascular: Flattening of the T-wave may be seen in electrocardiographic tracings.

Nervous System: The most serious adverse reactions reported in patients treated with oral metronidazole have been convulsive seizures, encephalopathy, aseptic meningitis, optic and peripheral neuropathy, the latter characterized mainly by numbness or paresthesia of an extremity. In addition, patients have reported syncope, vertigo, incoordination, ataxia, confusion, dysarthria, irritability, depression, weakness, and insomnia [see Warnings and Precautions (5.1)].

Gastrointestinal: Abdominal discomfort, nausea, vomiting, diarrhea, an unpleasant metallic taste, anorexia, epigastric distress, abdominal cramping, constipation, "furry" tongue, glossitis, stomatitis, pancreatitis, and modification of taste of alcoholic beverages.

Genitourinary: Overgrowth of Candida in the vagina, dyspareunia, decreased libido, proctitis.

Hematopoietic: Reversible neutropenia, reversible thrombocytopenia.

Hypersensitivity Reactions: Urticaria; erythematous rash; Stevens-Johnson Syndrome, toxic epidermal necrolysis, flushing; nasal congestion; dryness of the mouth, vagina, or vulva; fever; pruritus; fleeting joint pains [see Contraindications (4)].

Renal: Dysuria, cystitis, polyuria, incontinence, a sense of pelvic pressure, darkened urine.

7 DRUG INTERACTIONS

The intravaginal administration of a single dose of NUVESSA results in lower systemic exposure to metronidazole that is approximately 2% to 4% of that achieved following oral administration of 500 mg metronidazole tablets [see Clinical Pharmacology (12.3)] . The following drug interactions were reported for oral metronidazole.

7.1 Disulfiram

Use of oral metronidazole has been associated with psychotic reactions in alcoholic patients who are using disulfiram concurrently. NUVESSA should not be used by patients who have taken disulfiram within the last two weeks [see Contraindications (4.2)] .

7.2 Alcoholic Beverages

Use of oral metronidazole has been associated with a disulfiram-like reaction (abdominal cramps, nausea, vomiting, headaches, and flushing) to alcohol. Alcoholic beverages and preparations containing ethanol or propylene glycol should not be consumed during and for at least 24 hours after NUVESSA therapy [see Contraindications (4.3)].

7.3 Coumarin and Other Oral Anticoagulants

Use of oral metronidazole has been reported to potentiate the anticoagulant effect of warfarin and other coumarin anticoagulants, resulting in a prolongation of prothrombin time. This possible drug interaction should be considered when NUVESSA is prescribed for patients on this type of anticoagulant therapy.

7.4 Lithium

Short-term use of oral metronidazole has been associated with elevation of plasma lithium concentrations and, in a few cases, signs of lithium toxicity in patients stabilized on relatively high doses of lithium.

7.5 Cimetidine

Use of oral metronidazole with cimetidine may prolong the half-life and decrease plasma clearance of metronidazole. No dose adjustment of NUVESSA is necessary.

8 USE IN SPECIFIC POPULATIONS

8.1 Pregnancy

Risk Summary

There are no data available on the use of NUVESSA in pregnant women. Metronidazole usage in pregnancy has been associated with certain congenital anomalies (see Data) . In animal reproduction studies, no fetotoxicity or teratogenicity was observed when metronidazole was administered orally, during organogenesis to pregnant rats and rabbits at up to 30 times and 60 times the recommended human dose based on body surface area comparison, respectively (see Data) .

The estimated background risk of major birth defects and miscarriage for the indicated population is unknown. All pregnancies have a background risk of birth defect, loss, or other adverse outcomes. In the U.S. general population, the estimated background risk of major birth defects and miscarriage in clinically recognized pregnancies is 2 to 4% and 15 to 20%, respectively.

Data

Human Data

Blood levels following NUVESSA vaginal administration are lower than those achieved with oral metronidazole. Following a single intravaginal 5 g dose of NUVESSA, mean maximum concentration (Cmax) and total exposure (AUC0-∞) are approximately 2% and 4%, respectively, of those following a single oral 500 mg dose of metronidazole tablets [see Clinical Pharmacology (12.3)] . Metronidazole crosses the placental barrier and enters the fetal circulation rapidly.

There are published data from case-control studies, cohort studies, and 2 meta-analyses that include more than 5000 pregnant women who used metronidazole during pregnancy. Many studies included first trimester exposures. One study showed an increased risk of cleft lip, with or without cleft palate, in infants exposed to metronidazole in utero; however, these findings were not confirmed.

In addition, more than ten randomized placebo-controlled clinical trials enrolled more than 5000 pregnant women to assess the use of antibiotic treatment (including metronidazole) for bacterial vaginosis on the incidence of preterm delivery. Most studies did not show an increased risk for congenital anomalies or other adverse fetal outcomes following metronidazole exposure during pregnancy.

Three studies conducted to assess the risk of infant cancer following metronidazole exposure during pregnancy did not show an increased risk; however, the ability of these studies to detect such a signal was limited.

Animal Data

No fetotoxicity or teratogenicity was observed when metronidazole was administered orally to pregnant rabbits at up to 200 mg/kg (about 60 times the maximum human dose based on body surface area comparison). Similarly, no fetotoxic or teratogenic effects were observed in five studies in rats where dosing was administered orally in the diet or by gastric intubation at doses up to 200 mg/kg (about 30 times the maximum human dose based on body surface area comparison).

As well, no fetotoxicity or teratogenicity was observed when metronidazole was administered orally to pregnant mice at doses up to 100 mg/kg (about 7 times the maximum human dose based on body surface area comparison). However, some intrauterine deaths were observed in Swiss Webster mice administered metronidazole intraperitoneally at doses up to 15 mg/kg (about 1 times the maximum human dose based on body surface area comparison). The relationship of these intraperitoneal findings in mice to the vaginal use of NUVESSA is unknown.

8.2 Lactation

Risk Summary

There are no data on the presence of metronidazole in human milk following intravaginal administration. Metronidazole is present in human milk following oral metronidazole administration, at concentrations similar to those found in plasma (see Data). The metronidazole vaginal gel achieves 2% of the mean maximum serum concentration of a 500 mg oral metronidazole dose [see Clinical Pharmacology (12.3)] . The published literature reports no adverse effects in infants exposed through breastmilk to maternal orally administered metronidazole. There are no data on the effects on milk production.

Animal studies have shown the potential for tumorigenicity after oral metronidazole was administered chronically to rats and mice [see Nonclinical Toxicology (13.1)] . The clinical relevance of these findings is unclear. The developmental and health benefits of breastfeeding should be considered along with the mother’s clinical need for NUVESSA, and any potential adverse effects on the breastfed child from NUVESSA or from the underlying maternal condition. Alternatively, a lactating patient may interrupt breastfeeding and choose to pump and discard breastmilk during treatment with NUVESSA and for 48 hours after the last dose and feed her infant previously stored human milk or formula.

Data

In a study of lactating women receiving oral metronidazole 600 mg (n=11) or 1200 mg (n=4) daily, mean maternal plasma concentrations were 5.0 and 12.5 mcg/mL respectively, within 2 hours following administration; the milk: maternal plasma ratio was approximately 1.

8.4 Pediatric Use

The safety and effectiveness of NUVESSA have been established in pediatric subjects between the ages of 12 and less than 18 years old. Use of NUVESSA in this age group is supported by evidence from a multicenter, open-label safety and tolerability study in 60 pediatric patients with bacterial vaginosis [see Adverse Reactions (6.1)] and, evidence from adequate and well-controlled studies in adult women.

The safety and effectiveness of NUVESSA in pediatric subjects below the age of 12 years have not been established.

8.5 Geriatric Use

Clinical studies with NUVESSA did not include sufficient numbers of subjects 65 years of age or older to determine whether they respond differently than younger subjects.

10 OVERDOSAGE

There is no human experience with overdosage of metronidazole vaginal gel. Vaginally applied NUVESSA could be absorbed in sufficient amounts to produce systemic effects [see Warnings and Precautions (5) and Adverse Reactions (6.2)].

11 DESCRIPTION

NUVESSA contains 1.3% metronidazole, USP in a single-dose prefilled disposable applicator. It is intended for intravaginal use. Metronidazole is a nitroimidazole antimicrobial.

Chemically, metronidazole is a 2-methyl-5-nitroimidazole-1-ethanol. Its structural formula is:

The molecular formula is C6H9N3O3 with a molecular weight of 171.16.

NUVESSA is an aqueous gel containing metronidazole at a concentration of 13 mg/g (1.3%). The gel is formulated at pH 4.0. The gel also contains benzyl alcohol, methylparaben, polycarbophil, polyethylene glycol 400, propylene glycol, propylparaben, and purified water.

Each applicator contains approximately 65 mg of metronidazole in 5 g of vaginal gel.

12 CLINICAL PHARMACOLOGY

12.1 Mechanism of Action

Metronidazole is an antimicrobial drug [see Microbiology (12.4)].

12.3 Pharmacokinetics

Following a single, intravaginal 5 g dose of NUVESSA (equivalent to 65 mg of metronidazole) to 20 healthy female subjects, a mean maximum serum metronidazole concentration (Cmax) of 239 ng/mL was observed (range: 114 to 428 ng/mL). The average time to achieve this Cmax was 7.3 hours (range: 4 to 18 hours). This Cmax is approximately 2% of the mean maximum serum concentration reported in healthy subjects administered a single, oral 500 mg dose of metronidazole tablets (mean Cmax = 12,785 ng/mL).

The extent of exposure [area under the curve (AUC)] of metronidazole, when administered as a single intravaginal 5 g dose of NUVESSA (equivalent to 65 mg of metronidazole), was 5,434 ng∙hr/mL (range: 1382 to 12744 ng∙hr/mL). This AUC0-∞ is approximately 4% of the reported AUC of metronidazole following a single oral 500 mg dose of metronidazole (approximately 125,000 ng∙hr/mL).

12.4 Microbiology

Mechanism of Action
Metronidazole is a nitroimidazole antimicrobial agent that acts primarily against anaerobic bacteria and selected protozoa. The 5-nitro group on the metronidazole molecule is reduced by metabolically active anaerobes to its active state by the bacterial nitro-reductase enzyme after it diffuses into the bacterial cell. This results in the production of cytotoxic compounds that disrupt the helical structure of bacterial DNA thereby inhibiting bacterial nucleic acid synthesis which leads to cell death.

Resistance
The mechanism of resistance, like for other nitroimidazoles, appears to be multifactorial that include decreased uptake of the drug, higher efflux activity, and/or altered nitroreductase activity.

Antibacterial Activity
Culture and sensitivity testing of bacteria are not routinely performed to establish the diagnosis of bacterial vaginosis [see Clinical Studies (14)] . The following in vitro data are available, but their clinical significance is unknown. Metronidazole is active in vitro against most isolates of the following organisms reported to be associated with bacterial vaginosis:

Bacteroides spp.

Gardnerella vaginalis

Mobiluncus spp.

Peptostreptococcus spp.

13 NONCLINICAL TOXICOLOGY

13.1 Carcinogenesis Mutagenesis, Impairment of Fertility

Metronidazole has shown evidence of carcinogenic activity in a number of studies involving chronic oral administration in mice and rats. Pulmonary tumors were reported in several mouse studies in which mice were dosed orally at 75 mg/kg and above (about 6 or more times the maximum recommended human dose based on mg/m^2). Malignant lymphoma was reported at 66 mg/kg and above (about 5 or more times the maximum recommended human dose based on mg/m^2). These tumors have been observed in all six reported studies in the mouse, including one study in which the animals were dosed on an intermittent schedule (administration during every fourth week only). All these effects were statistically significant.

There were statistically significant increases in the incidence of mammary tumors, among female rats administered metronidazole at 270 mg/kg and above (about 40 times the maximum human dose based on mg/m^2). Hepatic adenomas and carcinomas were observed in rats administered 300 mg/kg (about 45 times the maximum human dose based on mg/m^2).

Two lifetime oral tumorigenicity studies in hamsters have been performed and reported to be negative at doses up to 80 mg/kg (about 10 times the maximum human dose based on mg/m^2).

Carcinogenesis studies have not been conducted with NUVESSA.

Although metronidazole has shown in vitro mutagenic activity in bacterial reverse mutation tests, it was negative in in vitro mammalian mutation systems including CHO/HGPRT and CH V79 lung cell assays. Metronidazole was not clastogenic in vitro chromosome aberration tests in CHO cells up to 5000 µg/mL but was positive in human and monkey peripheral blood lymphocytes at 0.1 µg/mL.

In general, numerous micronucleus studies in rats and mice have failed to demonstrate a potential for genetic damage up to single oral doses 3000 mg/kg in mice (about 225 times the maximum human dose based on mg/m^2). However, a dose dependent increase in the frequency of micronuclei was observed in CFW mice after intraperitoneal injections of up to 160 mg/kg (about 12 times the maximum human dose based on mg/m^2).

Fertility studies have been performed in mice orally dosed up to 500 mg/kg (about 37 times the maximum human dose based on mg/m^2) revealed no evidence of impaired fertility.

While no effects on fertility were observed in female rats dosed intraperitoneally at doses up to 1000 mg/kg (about 300 times the maximum human dose based on mg/m^2), studies in male rats resulted in effects on testes and sperm production at oral doses of 100 mg/kg and above (about 30 times the maximum human dose based on mg/m^2).

14 CLINICAL STUDIES

A single, randomized, double-blind, vehicle-controlled clinical trial was conducted to evaluate the efficacy of NUVESSA. Subjects had a clinical diagnosis of bacterial vaginosis defined by the presence of a homogenous vaginal discharge that (a) had a pH ≥ 4.7, (b) emitted a "fishy" amine odor when mixed with a 10% KOH solution ("whiff" test), and (c) contained clue cells ≥ 20% of the total vaginal epithelial cells. In addition, to be eligible for analysis subjects must have had a Gram stain Nugent score ≥ 4 and have been negative for N. gonorrhoeae and C. trachomatis. Non-pregnant females at least 18 years of age were randomized 1:1 to either NUVESSA or Vehicle Gel and instructed to administer study drug once at bedtime. Two hundred ninety-two (292) NUVESSA subjects and 285 Vehicle Gel subjects were eligible for the analysis.

Clinical cure was defined as (a) return of normal physiologic discharge, (b) negative KOH "whiff" test, and (c) clue cell < 20% of the total vaginal epithelial cells at the Test of Cure visit (between 21 to 30 days post-treatment). Bacteriological Cure was defined as a Nugent score of < 4 and Therapeutic cure was defined as clinical cure and bacteriological cure. NUVESSA demonstrated statistically significantly higher cure rates over Vehicle Gel as measured by clinical cure, bacteriological cure and therapeutic cure (Table 1).

Table 1. The Efficacy of NUVESSA for the Treatment of Bacterial Vaginosis in a Randomized, Double-Blind, Vehicle-Controlled, Parallel Group Study
Outcome | NUVESSA N = 292 n (%) | Vehicle Gel N = 285 n (%) | Treatment Difference (%) [95% Confidence Interval]
Test of Cure (Day 21 to 30)
Clinical Cure | 108 (37.0) | 76 (26.7) | 10.3 (2.8, 17.9)
Bacteriological Cure | 57 (19.5) | 22 (7.7) | 11.8 (6.3, 17.3)
Therapeutic Cure | 49 (16.8) | 18 (6.3) | 10.5 (5.3, 15.6)

Clinical Cure and Bacteriological Cure were also assessed at Day 7. Clinical Cure at Day 7 was achieved by a statistically significantly greater proportion of subjects in the NUVESSA group compared to subjects in the Vehicle Gel group (41.1% vs. 20.0%). Bacteriological Cure at Day 7 was achieved by a statistically significantly greater proportion of subjects in the NUVESSA group compared to subjects in the Vehicle Gel group (33.9% vs. 6.3%).

16 HOW SUPPLIED/STORAGE AND HANDLING

NUVESSA is available in cartons containing one single-dose, prefilled disposable applicator delivering 5 g of vaginal gel containing approximately 65 mg of metronidazole: 5 g disposable applicator (NDC 0642-7466-05).

STORAGE AND HANDLING

Store at 20-25°C (68-77°F); excursions permitted to 15°-30°C (59°-86°F) [ see USP Controlled Room temperature]. Do not freeze. Do not refrigerate.

17 PATIENT COUNSELING INFORMATION

Advise the patient to read the FDA-approved patient labeling (Patient Information and Instructions for Use).

Interaction with Alcohol
Instruct the patient not to consume alcoholic beverages and preparations containing ethanol or propylene glycol during and for at least 24 hours after treatment with NUVESSA [see Contraindications (4.3) and Drug Interactions (7.2)].

Drug Interactions
Instruct the patient not to use NUVESSA if disulfiram had been used within the last two weeks [see Contraindications (4.2)] , and to inform their healthcare provider if they are taking oral anticoagulants, or lithium [see Drug Interactions (7.3, 7.4)].

Vaginal Intercourse and Use with Vaginal Products
Instruct the patient not to engage in vaginal intercourse, or use other vaginal products (such as tampons or douches) following the single administration of NUVESSA.

Lactation
A patient may choose to pump and discard breast milk during treatment with NUVESSA and for 48 hours after last dose, and feed her infant previously stored human milk or formula [see Use in Specific Populations (8.2)].

Vaginal Irritation
Inform the patient to discontinue use and consult a healthcare provider if vaginal irritation occurs with use of NUVESSA.

Administration of Drug
Instruct the patient that NUVESSA is supplied as a single dose in a pre-filled applicator.

Distributed By:
Exeltis USA, Inc.
180 Park Ave.

Florham Park, NJ 07932

© 2022 Exeltis USA, Inc. All rights reserved.

NUVESSA® and its design are trademarks of Exeltis Healthcare S.L.

PATIENT INFORMATION
NUVESSA® (nue-ve-sa)
(metronidazole vaginal gel 1.3%)

For intravaginal use only. Do not use in the eyes, mouth or skin.

What is NUVESSA?
NUVESSA is a prescription medicine used to treat bacterial vaginal infections in females 12 years and older. It is not known if Nuvessa is safe and effective in female children younger than 12 years of age.

Do not use NUVESSA if you:

- are allergic to metronidazole, parabens, nitroimidazole derivatives, or any of the ingredients in NUVESSA. See the end of this leaflet for a complete list of ingredients in NUVESSA.
- take or have taken a medicine called Antabuse (disulfiram) in the last 2 weeks.
- drink alcohol. Do not drink alcohol while you use NUVESSA and for at least 24 hours after you stop using it. It can increase your chances of getting serious side effects.

Before you use NUVESSA, tell your healthcare provider about all your medical conditions, including if you:

- have or had central nervous system diseases.
- are pregnant or plan to become pregnant. It is not known if NUVESSA will harm your unborn baby. Tell your healthcare provider if you become pregnant during treatment with NUVESSA.
- are breastfeeding or plan to breastfeed. NUVESSA can pass into your breast milk. Talk with your healthcare provider about the best way to feed your baby while using NUVESSA.

Tell your healthcare provider all about the medicines you take, including prescription and over-the-counter medicines, vitamins and herbal supplements.

How should I use NUVESSA?

- See the " Instructions for Use" at the end of this Patient Information leaflet for detailed instructions about how to use NUVESSA.
- Use NUVESSA exactly as your healthcare provider tells you to.
- NUVESSA is used one time at bedtime.
- If you get NUVESSA in your eyes, rinse your eyes with cool tap water and call your healthcare provider.

What should I avoid while using NUVESSA?
Do not have vaginal intercourse or use other vaginal products (such as tampons or douches).

What are the possible side effects of NUVESSA?
The most common side effects of NUVESSA include: yeast infections, headache, vaginal itching, nausea, diarrhea, and pain with menstrual cycle and vaginal pain or discomfort. Tell your healthcare provider if you have any side effect that bothers you or that does not go away. These are not all the side effects of NUVESSA. For more information, ask your healthcare provider or pharmacist. Call your doctor for medical advice about side effects. You may report side effects to FDA at 1-800-FDA-1088.

General information about NUVESSA
Medicines are sometimes prescribed for purposes other than those listed in a Patient Information leaflet. Do not use NUVESSA for a condition for which it was not prescribed. Do not give NUVESSA to other people, even if they have the same symptoms that you have. It may harm them. You can ask your pharmacist or healthcare provider for information about NUVESSA that is written for health professionals.

What are the ingredients in NUVESSA?
Active ingredient: metronidazole
Inactive ingredients: polyethylene glycol 400, propylene glycol, benzyl alcohol, methylparaben, propylparaben, purified water, and polycarbophil

INSTRUCTIONS FOR USE

NUVESSA®
(metronidazole vaginal gel 1.3%)

For vaginal use only.

You will need the following supplies (See Figure A)

Figure A

Step 1: Remove the pre-filled applicator and plunger from the foil package (See Figure B)

- Tear open the foil packet just before using.
- Remove the pre-filled applicator and plunger from the foil packaging.

Figure B

Step 2: Insert the plunger into the open end of the pre-filled applicator (See Figure C)

- With the pink cap still on, push the tip of the plunger into the open end of the pre-filled applicator.

Figure C

Step 3: Remove the pink cap (See Figure D)

- Pull the pink cap straight off the top of the pre-filled applicator.

Figure D

Step 4: Prepare to insert the pre-filled applicator (See Figure E)

- The pre-filled applicator may be inserted while lying on your back with your knees bent or in any comfortable position.

Figure E

Step 5: Insert the pre-filled applicator (See Figure F)

- Hold the pre-filled applicator by the barrel and gently insert the rounded tip into your vagina as far as it will comfortably go, then pull back slightly.

Figure F

Step 6: Push the plunger (See Figure G)

- While holding the barrel in place, slowly press the plunger until it stops to release the gel into your vagina.

Figure G

Step 7: Remove the pre-filled applicator from your vagina and throw it away in your household trash.

How should I store NUVESSA?

- Store NUVESSA at room temperature between 68°F to 77°F (20°-25°C).
- Do not freeze.
- Do not refrigerate.

Keep NUVESSA and all medicines out of the reach of children.

This Patient Information and Instructions for Use have been approved by the US Food and Drug Administration.

Rx only

Distributed By:
Exeltis USA, Inc..
180 Park Ave., Florham Park, NJ 07932

© 2022 Exeltis USA, Inc. All rights reserved.

NUVESSA® and its design are trademarks of Exeltis Healthcare S.L.
Revised: 04/2022

PRINCIPAL DISPLAY PANEL - 5 g Applicator Carton

NDC 0642-7466-05

Exeltis

NUVESSA®
(metronidazole vaginal gel 1.3%)

FOR INTRAVAGINAL USE ONLY. Not for Ophthalmic, Dermal, or Oral Use.
Dosage: See package insert for dosage information.

SINGLE-DOSE
Net Wt. 5 g

Rx Only